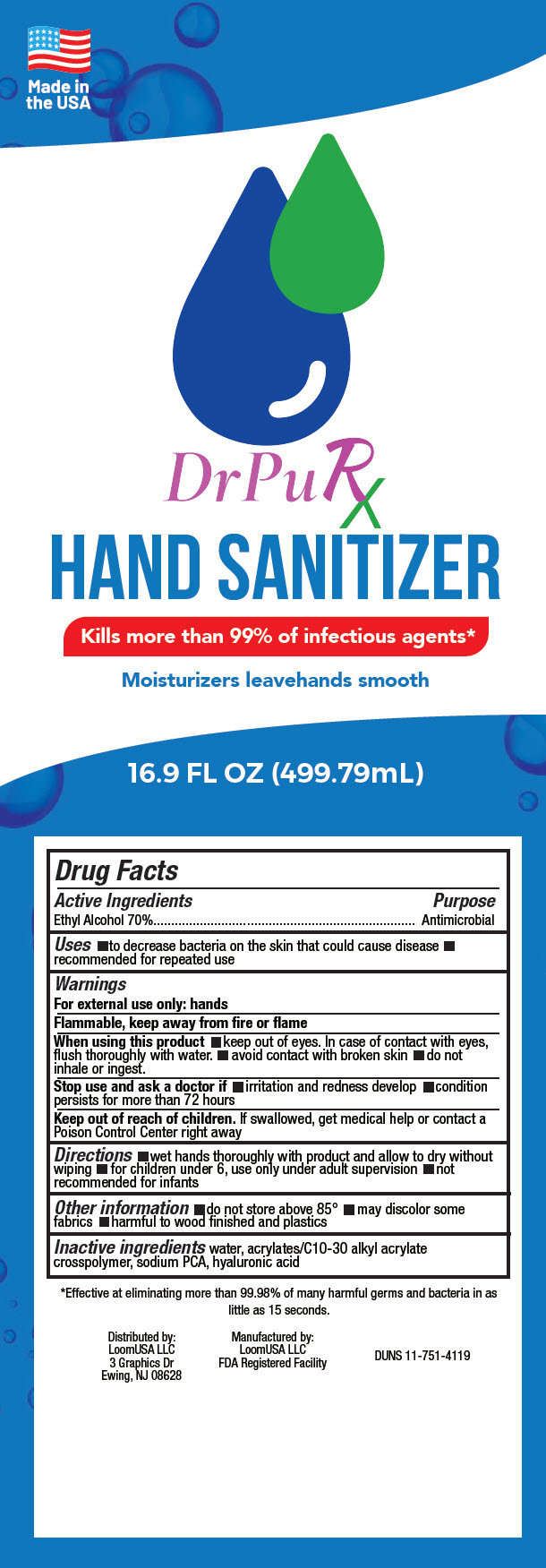 DRUG LABEL: DrPuRx HAND SANITIZER
NDC: 80607-921 | Form: GEL
Manufacturer: Loom USA
Category: otc | Type: HUMAN OTC DRUG LABEL
Date: 20220802

ACTIVE INGREDIENTS: ALCOHOL 70 mL/100 mL
INACTIVE INGREDIENTS: WATER; CARBOMER INTERPOLYMER TYPE A (ALLYL SUCROSE CROSSLINKED); SODIUM PYRROLIDONE CARBOXYLATE; HYALURONIC ACID

DrPuRx HAND SANITIZER

Drug Facts

Active Ingredients

Ethyl Alcohol 70%

Purpose

Antimicrobial

Uses

- to decrease bacteria on the skin that could cause disease
- recommended for repeated use

Warnings

For external use only: hands

Flammable, keep away from fire or flame

When using this product

- keep out of eyes. In case of contact with eyes, flush thoroughly with water.
- avoid contact with broken skin
- do not inhale or ingest.

Stop use and ask a doctor if

- irritation and redness develop
- condition persists for more than 72 hours

Keep out of reach of children. If swallowed, get medical help or contact a Poison Control Center right away

Directions

- wet hands thoroughly with product and allow to dry without wiping
- for children under 6, use only under adult supervision
- not recommended for infants

Other information

- do not store above 85°
- may discolor some fabrics
- harmful to wood finished and plastics

Inactive ingredients

water, acrylates/C10-30 alkyl acrylate crosspolymer, sodium PCA, hyaluronic acid

Distributed by:
LoomUSA LLC
3 Graphics Dr
Ewing, NJ 08628

Manufactured by:
LoomUSA LLC
FDA Registered Facility

PRINCIPAL DISPLAY PANEL - 499.79 mL Bottle Label

Made in
the USA

DrPuRX

HAND SANITIZER

Kills more than 99% of infectious agents*

Moisturizers leavehands smooth

16.9 FL OZ (499.79mL)